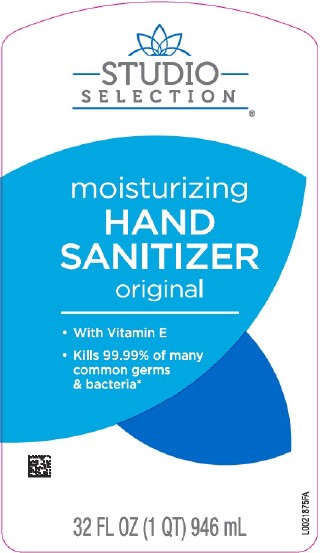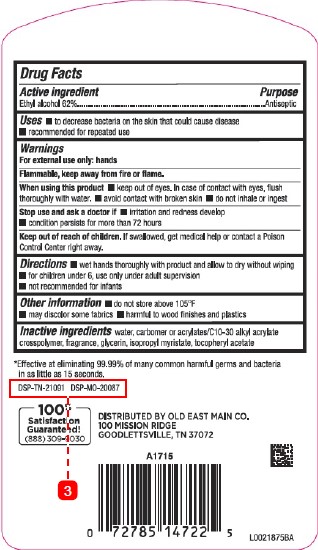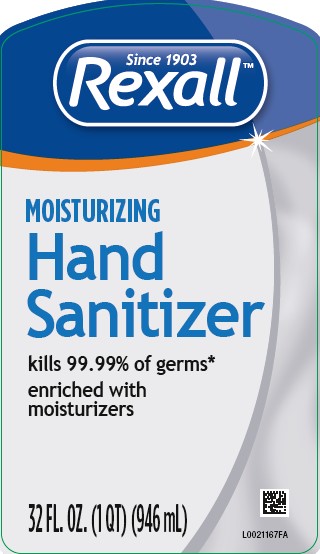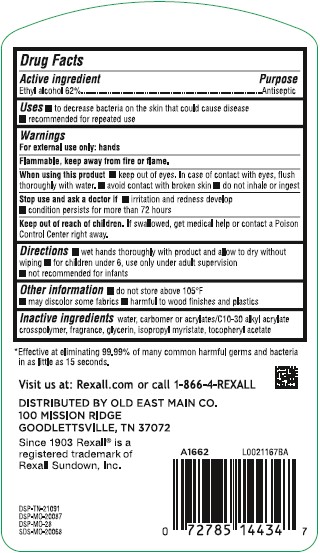 DRUG LABEL: Ethyl Alcohol
NDC: 75712-849 | Form: LIQUID
Manufacturer: Old East Main Co.
Category: otc | Type: HUMAN OTC DRUG LABEL
Date: 20260302

ACTIVE INGREDIENTS: ALCOHOL 62 mL/100 mL
INACTIVE INGREDIENTS: WATER; CARBOMER HOMOPOLYMER, UNSPECIFIED TYPE; CARBOMER INTERPOLYMER TYPE A (ALLYL SUCROSE CROSSLINKED); GLYCERIN; ISOPROPYL MYRISTATE; TOCOPHEROL

Studio Selection_Rexall 849.001/849AA-AG rev 0, rev 1 & 849BA
Moisturizing Hand Sanitizer

Active ingredient

Ethyl Alcohol 62%

Purpose

Antiseptic

Uses

- to decrease bacteria on the skin that could cause disease
- recommended for repeated use

Warnings

For exterenal use only: hands

Flammable, keep away from fire or flame.

When using this product

- keep out of eyes. In case of contact with eyes, flush thoroughly with water.
- avoid contact with broken skin
- do not inhale or ingest

Stop use and ask a doctor if

- irritation and redness develop
- condition persists for more than 72 hours

Keep out of reach of children.

If swallowed, get medical help or contact a Poison Control Center right away.

Directions

- wet hands thoroughly with product and allow to dry without wiping
- for children under 6, use only under adult supervision
- not recommended for infants

Other information

- do not store above 105⁰F
- may discolor some fabrics
- harmful to wood finishes and plastics

Inactive ingredients

water, carbomer or acrylates/C10-30 alkyl acrylate crosspolymer, fragrance, glycerin, isopropyl myristate, tocopheryl acetate

Claim

*Effective at eliminating 99.99% of many common harmful germs & bacteria in as little as 15 seconds.

ADVERSE REACTIONS SECTION

100% Satisfaction Guaranteed! (888)309-9030

DISTRIBUTED BY OLD EAST MAIN CO.

100 MISSION RIDGE

GOODLETTSVILLE, TN 37072

DSP-TN-21091 DSP-MO-20087

Principal display panel

STUDIO SELECTION®

moisturizing

HAND SANITIZER

original

- With Vitamin E
- kills 99.99% of germs & bacteria*

32 FL OZ (1 QT) 946 mL

Principal display panel

Since 1903

Rexall™

Moisturizing

Hand Sanitizer

Kills 99.99% of Germs*

enriched with moisturizers

32 FL. OZ. (1QT) (946 mL)